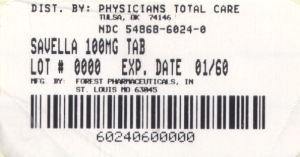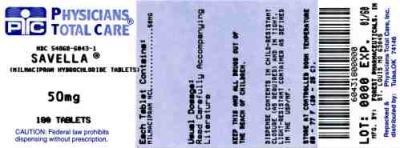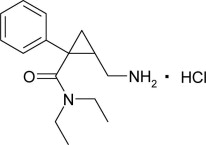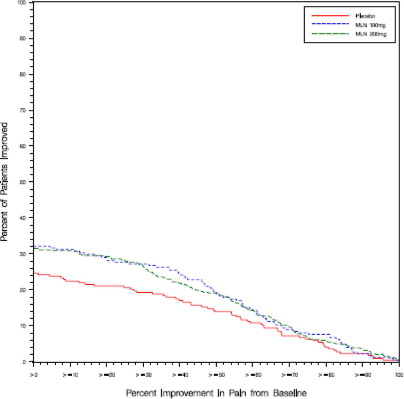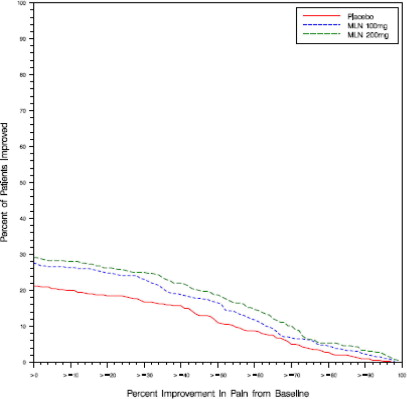 DRUG LABEL: Savella
NDC: 54868-6043 | Form: TABLET, FILM COATED
Manufacturer: Physicians Total Care, Inc.
Category: prescription | Type: HUMAN PRESCRIPTION DRUG LABEL
Date: 20111108

ACTIVE INGREDIENTS: milnacipran hydrochloride 50 mg/1 1
INACTIVE INGREDIENTS: dibasic calcium phosphate dihydrate; povidone; carboxymethylcellulose calcium; colloidal silicon dioxide; magnesium stearate; talc; FD&C Blue No. 1; FD&C Blue No. 2; FD&C Yellow No. 5; hypromelloses; polyethylene glycol; titanium dioxide

HIGHLIGHTS OF PRESCRIBING INFORMATION

These highlights do not include all the information needed to use Savella safely and effectively. See full prescribing information for Savella.
Savella® (milnacipran HCl) Tablets
Initial U.S. Approval: 2009

WARNING: SUICIDALITY AND ANTIDEPRESSANT DRUGS

See full prescribing information for complete boxed warning.

- Increased risk of suicidal ideation, thinking, and behavior in children, adolescents, and young adults taking antidepressants for major depressive disorder (MDD) and other psychiatric disorders. Savella is not approved for use in pediatric patients (5.1).

1 INDICATIONS AND USAGE

Savella® is a selective serotonin and norepinephrine reuptake inhibitor (SNRI) indicated for the management of fibromyalgia (1).

Savella is not approved for use in pediatric patients (5.1).

2 DOSAGE AND ADMINISTRATION

- Administer Savella in two divided doses per day (2.1).
- Based on efficacy and tolerability, dosing may be titrated according to the following schedule (2.1):
  Day 1: 12.5 mg once
  Days 2-3: 25 mg/day (12.5 mg twice daily)
  Days 4-7: 50 mg/day (25 mg twice daily)
  After Day 7: 100 mg/day (50 mg twice daily)
- Recommended dose is 100 mg/day (2.1).
- May be increased to 200 mg/day based on individual patient response (2.1).
- Dose should be adjusted in patients with severe renal impairment (2.2).

3 DOSAGE FORMS AND STRENGTHS

- Tablets: 12.5 mg, 25 mg, 50 mg, 100 mg (3)

4 CONTRAINDICATIONS

- Use of monoamine oxidase inhibitors concomitantly or in close temporal proximity (4.1).
- Use in patients with uncontrolled narrow-angle glaucoma (4.2).

5 WARNINGS AND PRECAUTIONS

- Suicidality: Monitor for worsening of depressive symptoms and suicide risk (5.1).
- Serotonin Syndrome or Neuroleptic Malignant Syndrome (NMS)-like Reactions: Serotonin syndrome or NMS-like reactions have been reported with SNRIs and SSRIs. Discontinue Savella and initiate supportive treatment (5.2, 7).
- Elevated blood pressure and heart rate: Cases have been reported with Savella. Monitor blood pressure and heart rate prior to initiating treatment with Savella and periodically throughout treatment (5.3, 5.4).
- Seizures: Cases have been reported with Savella therapy. Prescribe Savella with care in patients with a history of seizure disorder (5.5).
- Hepatotoxicity: More patients treated with Savella than with placebo experienced mild elevations of ALT and AST. Rarely, fulminant hepatitis has been reported in patients treated with Savella. Avoid concomitant use of Savella in patients with substantial alcohol use or chronic liver disease (5.6).
- Discontinuation: Withdrawal symptoms have been reported in patients when discontinuing treatment with Savella. A gradual dose reduction is recommended (5.7).
- Abnormal Bleeding: Savella may increase the risk of bleeding events. Caution patients about the risk of bleeding associated with the concomitant use of Savella and NSAIDs, aspirin, or other drugs that affect coagulation (5.9).
- Male patients with a history of obstructive uropathies may experience higher rates of genitourinary adverse events (5.11).

6 ADVERSE REACTIONS

The most frequently occurring adverse reactions (≥ 5% and greater than placebo) were nausea, headache, constipation, dizziness, insomnia, hot flush, hyperhidrosis, vomiting, palpitations, heart rate increased, dry mouth, and hypertension (6.3).

To report SUSPECTED ADVERSE REACTIONS, contact Forest Pharmaceuticals, Inc., at (800) 678-1605 or FDA at 1-800-FDA-1088 or www.fda.gov/medwatch.

7 DRUG INTERACTIONS

- Savella is unlikely to be involved in clinically significant pharmacokinetic drug interactions (7).
- Pharmacodynamic interactions of Savella with other drugs can occur (7).

8 USE IN SPECIFIC POPULATIONS

- Pregnancy and nursing mothers: Use only if the potential benefit justifies the potential risk to the fetus or child (8.1, 8.3).
- To enroll in the Savella Pregnancy Registry call 1-877-643-3010 (toll free) or download data forms from the registry website: www.savellapregnancyregistry.com (8.1).

FULL PRESCRIBING INFORMATION

WARNING: SUICIDALITY AND ANTIDEPRESSANT DRUGS

Savella is a selective serotonin and norepinephrine reuptake inhibitor (SNRI), similar to some drugs used for the treatment of depression and other psychiatric disorders. Antidepressants increased the risk compared to placebo of suicidal thinking and behavior (suicidality) in children, adolescents, and young adults in short-term studies of major depressive disorder (MDD) and other psychiatric disorders. Anyone considering the use of such drugs in a child, adolescent, or young adult must balance this risk with the clinical need. Short-term studies did not show an increase in the risk of suicidality with antidepressants compared to placebo in adults beyond age 24; there was a reduction in risk with antidepressants compared to placebo in adults aged 65 and older. Depression and certain other psychiatric disorders are themselves associated with increases in the risk of suicide. Patients of all ages who are started on Savella should be monitored appropriately and observed closely for clinical worsening, suicidality, or unusual changes in behavior. Families and caregivers should be advised of the need for close observation and communication with the prescriber. Savella is not approved for use in the treatment of major depressive disorder. Savella is not approved for use in pediatric patients [see Warnings and Precautions (5.1), Use in Specific Populations (8.4)].

1 INDICATIONS AND USAGE

Savella is indicated for the management of fibromyalgia.

Savella is not approved for use in pediatric patients [see Use in Specific Populations (8.4)].

2 DOSAGE AND ADMINISTRATION

Savella is given orally with or without food.

Taking Savella with food may improve the tolerability of the drug.

2.1 Recommended Dosing

The recommended dose of Savella is 100 mg/day (50 mg twice daily).

Based on efficacy and tolerability dosing may be titrated according to the following schedule:

Day 1: 12.5 mg once

Days 2-3: 25 mg/day (12.5 mg twice daily)

Days 4-7: 50 mg/day (25 mg twice daily)

After Day 7: 100 mg/day (50 mg twice daily)

Based on individual patient response, the dose may be increased to 200 mg/day (100 mg twice daily).

Doses above 200 mg/day have not been studied.

Savella should be tapered and not abruptly discontinued after extended use [see Discontinuing Savella (2.4) and Warnings and Precautions (5.7)]

2.2 Patients with Renal Insufficiency

No dosage adjustment is necessary in patients with mild renal impairment. Savella should be used with caution in patients with moderate renal impairment. For patients with severe renal impairment (indicated by an estimated creatinine clearance of 5-29 mL/min), the maintenance dose should be reduced by 50% to 50 mg/day (25 mg twice daily).

Based on individual patient response, the dose may be increased to 100 mg/day (50 mg twice daily).

Savella is not recommended for patients with end-stage renal disease.

2.3 Patients with Hepatic Insufficiency

No dosage adjustment is necessary for patients with hepatic impairment.

As with any drug, caution should be exercised in patients with severe hepatic impairment.

2.4 Discontinuing Savella

Withdrawal symptoms have been observed in clinical trials following discontinuation of milnacipran, as with other serotonin and norepinephrine re-uptake inhibitors (SNRIs) and selective serotonin re-uptake inhibitors (SSRIs). Patients should be monitored for these symptoms when discontinuing treatment. Savella should be tapered and not abruptly discontinued after extended use [see Warnings and Precautions (5.7)].

2.5 Switching patients to or from a Monoamine Oxidase Inhibitor (MAOI)

At least 14 days should elapse between discontinuation of a MAOI and initiation of therapy with Savella. In addition, at least 5 days should be allowed after stopping Savella before starting a MAOI [see Contraindications (4.1)].

3 DOSAGE FORMS AND STRENGTHS

Film-coated, immediate-release tablets in four strengths: 12.5 mg, 25 mg, 50 mg, and 100 mg of milnacipran hydrochloride.

12.5 mg tablets are round, blue, "F" on one side, "L" on the reverse;
25 mg tablets are round, white, "FL" on one side, "25" on the reverse;
50 mg tablets are oval, white, "FL" on one side, "50" on the reverse;
100 mg tablets are oval, pink, "FL" on one side, "100" on the reverse
[see Description (11) and How Supplied/ Storage and Handling (16)].

4 CONTRAINDICATIONS

4.1 Monoamine Oxidase Inhibitors

Concomitant use of Savella in patients taking monoamine oxidase inhibitors (MAOIs) is contraindicated. In patients receiving a serotonin reuptake inhibitor in combination with a monoamine oxidase inhibitor (MAOI), there have been reports of serious, sometimes fatal, reactions including hyperthermia, rigidity, myoclonus, autonomic instability with possible rapid fluctuations of vital signs, and mental status changes that include extreme agitation progressing to delirium and coma. These reactions have also been reported in patients who have recently discontinued serotonin reuptake inhibitors and have been started on an MAOI. Some cases presented with features resembling neuroleptic malignant syndrome. The effects of combined use of Savella and MAOIs have not been evaluated in humans. Therefore, it is recommended that Savella should not be used in combination with an MAOI, or within 14 days of discontinuing treatment with an MAOI. Similarly, at least 5 days should be allowed after stopping Savella before starting an MAOI [see Dosage and Administration (2.5), Warnings and Precautions (5.2)].

4.2 Uncontrolled Narrow-Angle Glaucoma

In clinical trials, Savella was associated with an increased risk of mydriasis. Mydriasis has been reported with other dual reuptake inhibitors of norepinephrine and serotonin; therefore, do not use Savella in patients with uncontrolled narrow-angle glaucoma.

5 WARNINGS AND PRECAUTIONS

5.1 Suicide Risk

Savella is a selective serotonin and norepinephrine re-uptake inhibitor (SNRI), similar to some drugs used for the treatment of depression and other psychiatric disorders.

Patients, both adult and pediatric, with depression or other psychiatric disorders may experience worsening of their depression and/or the emergence of suicidal ideation and behavior (suicidality) or unusual changes in behavior, whether or not they are taking these medications, and this risk may persist until significant remission occurs. Suicide is a known risk of depression and certain other psychiatric disorders, and these disorders themselves are the strongest predictors of suicide. There has been a long-standing concern, however, that antidepressants, including drugs that inhibit the reuptake of norepinephrine and/or serotonin, may have a role in inducing worsening of depression and the emergence of suicidality in certain patients during the early phases of treatment.

In the placebo-controlled clinical trials of adults with fibromyalgia, among the patients who had a history of depression at treatment initiation, the incidence of suicidal ideation was 0.5% in patients treated with placebo, 0% in patients treated with Savella 100 mg/day, and 1.3% in patients treated with Savella 200 mg/day. No suicides occurred in the short-term or longer-term (up to 1 year) fibromyalgia trials.

Pooled analyses of short-term placebo-controlled trials of drugs used to treat depression (SSRIs and others) showed that these drugs increase the risk of suicidal thinking and behavior (suicidality) in children, adolescents, and young adults (ages 18-24) with major depressive disorder (MDD) and other psychiatric disorders. Short-term studies did not show an increase in the risk of suicidality with these drugs compared to placebo in adults beyond age 24; there was a reduction in suicidality risk with antidepressants compared to placebo in adults age 65 and older.

The pooled analyses of placebo-controlled trials in children and adolescents with MDD, obsessive compulsive disorder (OCD), or other psychiatric disorders included a total of 24 short-term trials of 9 drugs used to treat depression in over 4400 patients. The pooled analyses of placebo-controlled trials in adults with MDD or other psychiatric disorders included a total of 295 short-term trials (median duration of 2 months) of 11 antidepressant drugs in over 77,000 patients. There was considerable variation in risk of suicidality among drugs, but a tendency toward an increase in the younger patients for almost all drugs studied. There were differences in absolute risk of suicidality across the different indications, with the highest incidence in MDD. The risk of differences (drug versus placebo), however, were relatively stable within age strata and across indications. These risk differences (drug-placebo difference in the number of cases of suicidality per 1000 patients treated) are provided in Table 1.

Table 1. Risk Differences (Drug - Placebo) in the number of Cases of Suicidality, per 1000 patients treated
Age Range | Drug-Placebo Difference in Number of Cases of Suicidality per 1000 Patients Treated
< 18 | 14 additional cases
18-24 | 5 additional cases
 | Decreases Compared to Placebo
25-64 | 1 fewer case
≥ 65 | 6 fewer cases

No suicides occurred in any of the pediatric trials. There were suicides in the adult trials, but the number was not sufficient to reach any conclusion about drug effect on suicide.

It is unknown whether the suicidality risk extends to longer-term use, i.e., beyond several months. However, there is substantial evidence from placebo-controlled maintenance trials in adults with depression that the use of antidepressants can delay the recurrence of depression.

All patients being treated with drugs inhibiting the reuptake of norepinephrine and/or serotonin for any indication should be monitored appropriately and observed closely for clinical worsening, suicidality, and unusual changes in behavior, especially during the initial few months of a course of drug therapy, or at times of dose changes, either increases or decreases.

The following symptoms, anxiety, agitation, panic attacks, insomnia, irritability, hostility, aggressiveness, impulsivity, akathisia (psychomotor restlessness), hypomania, mania, have been reported in adult and pediatric patients being treated with drugs inhibiting the reuptake of norepinephrine and/or serotonin for major depressive disorder as well as for other indications, both psychiatric and nonpsychiatric. Although a causal link between the emergence of such symptoms and either the worsening of depression and/or the emergence of suicidal impulses has not been established, there is concern that such symptoms may represent precursors to emerging suicidality.

Consideration should be given to changing the therapeutic regimen, including possibly discontinuing the medication, in patients who may experience worsening depressive symptoms, or who are experiencing emergent suicidality or symptoms that might be precursors to worsening depression or suicidality, especially if these symptoms are severe or abrupt in onset, or were not part of the patient's presenting symptoms.

If the decision has been made to discontinue treatment due to worsening depressive symptoms or emergent suicidality, medication should be tapered, as rapidly as is feasible, but with recognition that abrupt discontinuation can produce withdrawal symptoms [see Dosage and Administration (2.1, 2.4), and Warnings and Precautions (5.7)].

Families and caregivers of patients being treated with drugs inhibiting the reuptake of norepinephrine and/or serotonin for major depressive disorder or other indications, both psychiatric and nonpsychiatric, should be alerted about the need to monitor patients for the emergence of agitation, irritability, unusual changes in behavior, and the other symptoms described above, as well as the emergence of suicidality, and to report such symptoms immediately to health care providers. Such monitoring should include daily observation by families and caregivers. Prescriptions for Savella should be written for the smallest quantity of tablets consistent with good patient management, in order to reduce the risk of overdose.

5.2 Serotonin Syndrome or Neuroleptic Malignant Syndrome (NMS)-Like Reactions

The development of a potentially life-threatening serotonin syndrome or Neuroleptic Malignant Syndrome (NMS)-like reactions have been reported with SNRIs and SSRIs alone, including Savella, but particularly with concomitant use of serotonergic drugs (including triptans), with drugs which impair metabolism of serotonin (including MAOIs) or with antipsychotics or other dopamine antagonists. Serotonin syndrome symptoms may include mental status changes (e.g., agitation, hallucinations, coma), autonomic instability (e.g., tachycardia, labile blood pressure, hyperthermia), neuromuscular aberrations (e.g., hyperreflexia, incoordination) and/or gastrointestinal symptoms (e.g., nausea, vomiting, diarrhea) [see Drug Interactions (7)]. Serotonin syndrome, in its most severe form, can resemble neuroleptic malignant syndrome, which includes hyperthermia, muscle rigidity, autonomic instability with possible rapid fluctuation of vital signs, and mental status changes. Patients should be monitored for the emergence of serotonin syndrome or NMS-like signs and symptoms. The concomitant use of Savella with MAOIs is contraindicated [see Contraindications (4.1)].

If concomitant treatment of Savella with a 5-hydroxytryptamine receptor agonist (triptan) is clinically warranted, careful observation of the patient is advised, particularly during treatment initiation and dose increases [see Drug Interactions (7)].

The concomitant use of Savella with serotonin precursors (such as tryptophan) is not recommended [see Drug Interactions (7)]. Treatment with Savella and any concomitant serotonergic or antidopaminergic agents, including antipsychotics, should be discontinued immediately if the above events occur, and supportive symptomatic treatment should be initiated.

5.3 Effects on Blood Pressure

Inhibition of the reuptake of norepinephrine (NE) and serotonin (5-HT) can lead to cardiovascular effects. SNRIs, including Savella, have been associated with reports of increase in blood pressure.

In a double-blind, placebo-controlled clinical pharmacology study in healthy subjects designed to evaluate the effects of milnacipran on various parameters, including blood pressure at supratherapeutic doses, there was evidence of mean increases in supine blood pressure at doses up to 300 mg twice daily (600 mg/day). At the highest 300 mg twice daily dose, the mean increase in systolic blood pressure was up to 8.1 mm Hg for the placebo group and up to 10.0 mm Hg for the Savella treated group over the 12 hour steady state dosing interval. The corresponding mean increase in diastolic blood pressure over this interval was up to 4.6 mm Hg for placebo and up to 11.5 mm Hg for the Savella treated group.

In the 3-month placebo-controlled fibromyalgia clinical trials, Savella treatment was associated with mean increases of up to 3.1 mm Hg in systolic blood pressure (SBP) and diastolic blood pressure (DBP) [see Adverse Reactions (6.3)].

In the placebo-controlled trials, among fibromyalgia patients who were non-hypertensive at baseline, approximately twice as many patients in the Savella treatment arms became hypertensive at the end of the study (SBP ≥ 140 mmHg or DBP ≥ 90 mmHg) compared with the placebo patients: 7.2% of patients in the placebo arm versus 19.5% of patients treated with Savella 100 mg/day and 16.6% of patients treated with Savella 200 mg/day. Among patients who met systolic criteria for pre-hypertension at baseline (SBP 120-139 mmHg), more patients became hypertensive at the end of the study in the Savella treatment arms than placebo: 9% of patients in the placebo arm versus 14% in both the Savella 100 mg/day and the Savella 200 mg/day treatment arms.

Among fibromyalgia patients who were hypertensive at baseline, more patients in the Savella treatment arms had a >15 mmHg increase in SBP than placebo at the end of the study: 1% of patients in the placebo arm versus 7% in the Savella 100 mg/day and 2% in the Savella 200 mg/day treatment arms. Similarly, more patients who were hypertensive at baseline and were treated with Savella had DBP increases > 10 mmHg than placebo at the end of study: 3% of patients in the placebo arm versus 8% in the Savella 100 mg/day and 6% in the Savella 200 mg/day treatment arms.

Sustained increases in SBP (increase of ≥ 15 mmHg on three consecutive post-baseline visits) occurred in 2% of placebo patients versus 9% of patients receiving Savella 100 mg/day and 6% of patients receiving Savella 200 mg/day. Sustained increases in DBP (increase of ≥ 10 mmHg on 3 consecutive post-baseline visits) occurred in 4% of patients receiving placebo versus 13% of patients receiving Savella 100 mg/day and 10% of patients receiving Savella 200 mg/day.

Sustained increases in blood pressure could have adverse consequences. Cases of elevated blood pressure requiring immediate treatment have been reported.

Concomitant use of Savella with drugs that increase blood pressure and pulse has not been evaluated and such combinations should be used with caution [see Drug Interactions (7)].

Effects of Savella on blood pressure in patients with significant hypertension or cardiac disease have not been systematically evaluated. Savella should be used with caution in these patients.

Blood pressure should be measured prior to initiating treatment and periodically measured throughout Savella treatment. Pre-existing hypertension and other cardiovascular disease should be treated before starting therapy with Savella. For patients who experience a sustained increase in blood pressure while receiving Savella, either dose reduction or discontinuation should be considered.

5.4 Effects on Heart Rate

SNRIs have been associated with reports of increase in heart rate.

In clinical trials, relative to placebo, Savella treatment was associated with mean increases in pulse rate of approximately 7 to 8 beats per minute [see Adverse Reactions (6.2, 6.3)].

Increases in pulse ≥ 20 bpm occurred more frequently in Savella-treated patients when compared to placebo: 0.3% in the placebo arm versus 8% in the Savella 100 mg/day and 8% in the 200 mg/day treatment arms. The effect of Savella on heart rate did not appear to increase with increasing dose.

Savella has not been systematically evaluated in patients with a cardiac rhythm disorder.

Heart rate should be measured prior to initiating treatment and periodically measured throughout Savella treatment. Pre-existing tachyarrhythmias and other cardiac disease should be treated before starting therapy with Savella. For patients who experience a sustained increase in heart rate while receiving Savella, either dose reduction or discontinuation should be considered.

5.5 Seizures

Savella has not been systematically evaluated in patients with a seizure disorder. In clinical trials evaluating Savella in patients with fibromyalgia, seizures/convulsions have not been reported. However, seizures have been reported infrequently in patients treated with Savella for disorders other than fibromyalgia. Savella should be prescribed with care in patients with a history of a seizure disorder.

5.6 Hepatotoxicity

In the placebo-controlled fibromyalgia trials, increases in the number of patients treated with Savella with mild elevations of ALT or AST (1-3 times the upper limit of normal, ULN) were observed. Increases in ALT were more frequently observed in the patients treated with Savella 100 mg/day (6%) and Savella 200 mg/day (7%), compared to the patients treated with placebo (3%). One patient receiving Savella 100 mg/day (0.2%) had an increase in ALT greater than 5 times the upper limit of normal but did not exceed 10 times the upper limit of normal. Increases in AST were more frequently observed in the patients treated with Savella 100 mg/day (3%) and Savella 200 mg/day (5%) compared to the patients treated with placebo (2%).

The increases of bilirubin observed in the fibromyalgia clinical trials were not clinically significant.

No case met the criteria of elevated ALT > 3x ULN and associated with an increase in bilirubin ≥ 2x ULN.

There have been cases of increased liver enzymes and reports of severe liver injury, including fulminant hepatitis with milnacipran from foreign postmarketing experience. In the cases of severe liver injury, there were significant underlying clinical conditions and/or the use of multiple concomitant medications. Because of underreporting, it is impossible to provide an accurate estimate of the true incidence of these reactions.

Savella should be discontinued in patients who develop jaundice or other evidence of liver dysfunction. Treatment with Savella should not be resumed unless another cause can be established.

Savella should ordinarily not be prescribed to patients with substantial alcohol use or evidence of chronic liver disease.

5.7 Discontinuation of Treatment with Savella

Withdrawal symptoms have been observed in clinical trials following discontinuation of milnacipran, as with other SNRIs and SSRIs.

During marketing of milnacipran, and other SNRIs and SSRIs, there have been spontaneous reports of adverse events indicative of withdrawal and physical dependence occurring upon discontinuation of these drugs, particularly when discontinuation is abrupt. The adverse events include the following: dysphoric mood, irritability, agitation, dizziness, sensory disturbances (e.g., paresthesias such as electric shock sensations), anxiety, confusion, headache, lethargy, emotional lability, insomnia, hypomania, tinnitus, and seizures. Although these events are generally self-limiting, some have been reported to be severe.

Patients should be monitored for these symptoms when discontinuing treatment with Savella. Savella should be tapered and not abruptly discontinued after extended use. If intolerable symptoms occur following a decrease in the dose or upon discontinuation of treatment, then resuming the previously prescribed dose may be considered. Subsequently, the physician may continue decreasing the dose but at a more gradual rate [see Dosage and Administration (2.4)].

5.8 Hyponatremia

Hyponatremia may occur as a result of treatment with SSRIs and SNRIs, including Savella. In many cases, this hyponatremia appears to be the result of the syndrome of inappropriate antidiuretic hormone secretion (SIADH). Cases with serum sodium lower than 110 mmol/L have been reported. Elderly patients may be at greater risk of developing hyponatremia with SNRIs, SSRIs, or Savella. Also, patients taking diuretics or who are otherwise volume-depleted may be at greater risk [see Geriatric Use (8.5)]. Discontinuation of Savella should be considered in patients with symptomatic hyponatremia.

Signs and symptoms of hyponatremia include headache, difficulty concentrating, memory impairment, confusion, weakness, and unsteadiness, which may lead to falls. Signs and symptoms associated with more severe and/or acute cases have included hallucination, syncope, seizure, coma, respiratory arrest, and death.

5.9 Abnormal Bleeding

SSRIs and SNRIs, including Savella, may increase the risk of bleeding events. Concomitant use of aspirin, nonsteroidal anti-inflammatory drugs, warfarin, and other anti-coagulants may add to this risk. Case reports and epidemiological studies (case-control and cohort design) have demonstrated an association between use of drugs that interfere with serotonin reuptake and the occurrence of gastrointestinal bleeding. Bleeding events related to SSRIs and SNRIs use have ranged from ecchymoses, hematomas, epistaxis, and petechiae to life-threatening hemorrhages.

Patients should be cautioned about the risk of bleeding associated with the concomitant use of Savella and NSAIDs, aspirin, or other drugs that affect coagulation.

5.10 Activation of Mania

No activation of mania or hypomania was reported in the clinical trials evaluating effects of Savella in patients with fibromyalgia. However those clinical trials excluded patients with current major depressive episode. Activation of mania and hypomania have been reported in patients with mood disorders who were treated with other similar drugs for major depressive disorder. As with these other agents, Savella should be used cautiously in patients with a history of mania.

5.11 Patients with a History of Dysuria

Because of their noradrenergic effect, SNRIs including Savella, can affect urethral resistance and micturition. In the controlled fibromyalgia trials, dysuria occurred more frequently in patients treated with Savella (1%) than in placebo-treated patients (0.5%). Caution is advised in use of Savella in patients with a history of dysuria, notably in male patients with prostatic hypertrophy, prostatitis, and other lower urinary tract obstructive disorders. Male patients are more prone to genitourinary adverse effects, such as dysuria or urinary retention, and may experience testicular pain or ejaculation disorders.

5.12 Controlled Narrow-Angle Glaucoma

Mydriasis has been reported in association with SNRIs and Savella; therefore, Savella should be used cautiously in patients with controlled narrow-angle glaucoma.

Do not use Savella in patients with Uncontrolled Narrow-Angle Glaucoma [see Contraindications (4.2)].

5.13 Concomitant Use with Alcohol

In clinical trials, more patients treated with Savella developed elevated transaminases than did placebo treated patients [see Warnings and Precautions (5.6)]. Because it is possible that milnacipran may aggravate pre-existing liver disease, Savella should not be prescribed to patients with substantial alcohol use or evidence of chronic liver disease.

6 ADVERSE REACTIONS

6.1 Clinical Trial Data Sources

Savella was evaluated in three double-blind placebo-controlled trials involving 2209 fibromyalgia patients (1557 patients treated with Savella and 652 patients treated with placebo) for a treatment period up to 29 weeks.

The stated frequencies of adverse reactions represent the proportion of individuals who experienced, at least once, a treatment-emergent adverse reaction of the type listed. A reaction was considered treatment emergent if it occurred for the first time or worsened while receiving therapy following baseline evaluation.

Because clinical trials are conducted under widely varying conditions, adverse reaction rates observed in the clinical trials of a drug cannot be directly compared to rates in the clinical trials of another drug and may not reflect the rates observed in practice.

6.2 Adverse Reactions Leading to Discontinuation

In placebo-controlled trials in patients with fibromyalgia, 23% of patients treated with Savella 100 mg/day, 26% of patients treated with Savella 200 mg/day discontinued prematurely due to adverse reactions, compared to 12% of patients treated with placebo. The adverse reactions that led to withdrawal in ≥ 1% of patients in the Savella treatment group and with an incidence rate greater than that in the placebo treatment group were nausea (milnacipran 6%, placebo 1%), palpitations (milnacipran 3%, placebo 1%), headache (milnacipran 2%, placebo 0%), constipation (milnacipran 1%, placebo 0%), heart rate increased (milnacipran 1%, placebo 0%), hyperhidrosis (milnacipran 1%, placebo 0%), vomiting (milnacipran 1%, placebo 0%), and dizziness (milnacipran 1% and placebo 0.5%). Discontinuation due to adverse reactions was generally more common among patients treated with Savella 200 mg/day compared to Savella 100 mg/day.

6.3 Most Common Adverse Reactions

In the placebo-controlled fibromyalgia patient trials, the most frequently occurring adverse reaction in clinical trials was nausea. The most common adverse reactions (incidence ≥ 5% and twice placebo) in patients treated with Savella were constipation, hot flush, hyperhidrosis, vomiting, palpitations, heart rate increased, dry mouth, and hypertension.

Table 2 lists all adverse reactions that occurred in at least 2% of patients treated with Savella at either 100 or 200 mg/day and at an incidence greater than that of placebo.

Table 2. Treatment-Emergent Adverse Reaction Incidence in Placebo Controlled Trials in Fibromyalgia Patients (Events Occurring in at Least 2% of All Savella-Treated Patients and Occurring More Frequently in Either Savella Treatment Group Than in the Placebo Treatment Group)
System Organ Class-Preferred Term | Savella 100 mg/day (n = 623)% | Savella 200 mg/day (n = 934) % | All Savella (n = 1557)% | Placebo (n = 652)%
Cardiac Disorders
Palpitations | 8 | 7 | 7 | 2
Tachycardia | 3 | 2 | 2 | 1
Eye Disorders
Vision blurred | 1 | 2 | 2 | 1
Gastrointestinal Disorders
Nausea | 35 | 39 | 37 | 20
Constipation | 16 | 15 | 16 | 4
Vomiting | 6 | 7 | 7 | 2
Dry mouth | 5 | 5 | 5 | 2
Abdominal pain | 3 | 3 | 3 | 2
General Disorders
Chest pain | 3 | 2 | 2 | 2
Chills | 1 | 2 | 2 | 0
Chest discomfort | 2 | 1 | 1 | 1
Infections
Upper respiratory tract infection | 7 | 6 | 6 | 6
Investigations
Heart rate increased | 5 | 6 | 6 | 1
Blood pressure increased | 3 | 3 | 3 | 1
Metabolism and Nutrition Disorders
Decreased appetite | 1 | 2 | 2 | 0
Nervous System Disorders
Headache | 19 | 17 | 18 | 14
Dizziness | 11 | 10 | 10 | 6
Migraine | 6 | 4 | 5 | 3
Paresthesia | 2 | 3 | 2 | 2
Tremor | 2 | 2 | 2 | 1
Hypoesthesia | 1 | 2 | 1 | 1
Tension headache | 2 | 1 | 1 | 1
Psychiatric Disorders
Insomnia | 12 | 12 | 12 | 10
Anxiety | 5 | 3 | 4 | 4
Respiratory Disorders
Dyspnea | 2 | 2 | 2 | 1
Skin Disorders
Hyperhidrosis | 8 | 9 | 9 | 2
Rash | 3 | 4 | 3 | 2
Pruritus | 3 | 2 | 2 | 2
Vascular Disorders
Hot flush | 11 | 12 | 12 | 2
Hypertension | 7 | 4 | 5 | 2
Flushing | 2 | 3 | 3 | 1

6.4 Weight Changes

In placebo-controlled fibromyalgia clinical trials, patients treated with Savella for up to 3 months experienced a mean weight loss of approximately 0.8 kg in both the Savella 100 mg/day and the Savella 200 mg/day treatment groups, compared with a mean weight loss of approximately 0.2 kg in placebo-treated patients.

6.5 Genitourinary Adverse Reactions in Males

In the placebo-controlled fibromyalgia studies, the following treatment-emergent adverse reactions related to the genitourinary system were observed in at least 2% of male patients treated with Savella, and occurred at a rate greater than in placebo-treated male patients: dysuria, ejaculation disorder, erectile dysfunction, ejaculation failure, libido decreased, prostatitis, scrotal pain, testicular pain, testicular swelling, urinary hesitation, urinary retention, urethral pain, and urine flow decreased.

6.6 Other Adverse Reactions Observed During Clinical Trials of Savella in Fibromyalgia

Following is a list of frequent (those occurring on one or more occasions in at least 1/100 patients) treatment-emergent adverse reactions reported from 1824 fibromyalgia patients treated with Savella for periods up to 68 weeks. The listing does not include those events already listed in Table 2, those events for which a drug cause was remote, those events which were so general as to be uninformative, and those events reported only once which did not have a substantial probability of being acutely life threatening.

Adverse reactions are categorized by body system and listed in order of decreasing frequency. Adverse reactions of major clinical importance are described in the Warnings and Precautions section (5).

Gastrointestinal Disorders — diarrhea, dyspepsia, gastroesophageal reflux disease, flatulence, abdominal distension

General Disorders — fatigue, peripheral edema, irritability, pyrexia

Infections — urinary tract infection, cystitis

Injury, Poisoning, and Procedural Complications — contusion, fall

Investigations — weight decreased or increased

Metabolism and Nutrition Disorders — hypercholesterolemia

Nervous System Disorders — somnolence, dysgeusia

Psychiatric Disorders — depression, stress

Skin Disorders — night sweats

6.7 Postmarketing Spontaneous Reports

The following additional adverse reactions have been identified from spontaneous reports of Savella received worldwide. These adverse reactions have been chosen for inclusion because of a combination of seriousness, frequency of reporting, or potential causal connection to Savella. However, because these adverse reactions were reported voluntarily from a population of uncertain size, it is not always possible to reliably estimate their frequency or establish a causal relationship to drug exposure. These events include:

Blood and Lymphatic System Disorders — leukopenia, neutropenia, thrombocytopenia

Cardiac Disorders — supraventricular tachycardia

Eye Disorders — accommodation disorder

Endocrine Disorders — hyperprolactinemia

Hepatobiliary Disorders — hepatitis

Metabolism and Nutrition Disorders — anorexia, hyponatremia

Musculoskeletal and Connective Tissue Disorders — rhabdomyolysis

Nervous System Disorders — convulsions (including grand mal), loss of consciousness,

Parkinsonism

Psychiatric Disorders — delirium, hallucination

Renal and Urinary Disorders — acute renal failure

Reproductive System and Breast Disorders — galactorrhea

Skin Disorders — erythema multiforme, Stevens Johnson syndrome

Vascular Disorders — hypertensive crisis

7 DRUG INTERACTIONS

Milnacipran undergoes minimal CYP450 related metabolism, with the majority of the dose excreted unchanged in urine (55%), and has a low binding to plasma proteins (13%). In vitro and in vivo studies showed that Savella is unlikely to be involved in clinically significant pharmacokinetic drug interactions [see Pharmacokinetics in Special Populations (12.4)].

7.1 Monoamine Oxidase Inhibitors

[See Contraindications (4.1)]

7.2 Serotonergic Drugs

Due to the mechanism of action of SNRIs and SSRIs, including Savella, and the potential for serotonin syndrome or Neuroleptic Malignant Syndrome (NMS) - like reactions, caution is advised when Savella is co-administered with other drugs that may affect the serotonergic neurotransmitter systems. This includes drugs such as triptans, lithium, tryptophan, antipsychotics and dopamine antagonists.

Co-administration of Savella with other inhibitors of serotonin re-uptake may result in hypertension and coronary artery vasoconstriction, through additive serotonergic effects. Concomitant use of Savella with other SSRIs, SNRIs, or tryptophan is not recommended [see Warnings and Precautions (5.2)].

7.3 Triptans

There have been rare postmarketing reports of serotonin syndrome with use of an SSRI and a triptan. If concomitant treatment of Savella with a triptan is clinically warranted, careful observation of the patient is advised, particularly during treatment initiation and dose increases [see Warnings and Precautions (5.2)].

7.4 Catecholamines

Savella inhibits the reuptake of norepinephrine. Therefore concomitant use of Savella with epinephrine and norepinephrine may be associated with paroxysmal hypertension and possible arrhythmia [see Warnings and Precautions (5.3, 5.4)].

7.5 CNS-active drugs

Given the primary CNS effects of Savella, caution should be used when it is taken in combination with other centrally acting drugs, including those with a similar mechanism of action.

Clomipramine: In a drug-drug interaction study, an increase in euphoria and postural hypotension was observed in patients who switched from clomipramine to Savella.

7.6 Clinically Important Interactions with Select Cardiovascular Agents

Digoxin: Use of Savella concomitantly with digoxin may be associated with potentiation of adverse hemodynamic effects. Postural hypotension and tachycardia have been reported in combination therapy with intravenously administered digoxin (1 mg). Co-administration of Savella and intravenous digoxin should be avoided [see Warnings and Precautions (5.3, 5.4)].

Clonidine: Because Savella inhibits norepinephrine reuptake, co-administration with clonidine may inhibit clonidine's anti-hypertensive effect.

8 USE IN SPECIFIC POPULATIONS

8.1 Pregnancy

Pregnancy Category C

Milnacipran increased the incidence of dead fetuses in utero in rats at doses of 5 mg/kg/day (0.25 times the MRHD on a mg/m^2 basis). Administration of milnacipran to mice and rabbits during the period of organogenesis did not result in embryotoxicity or teratogenicity at doses up to 125 mg/kg/day in mice (3 times the maximum recommended human dose [MRHD] of 200 mg/day on a mg/m^2 basis) and up to 60 mg/kg/day in rabbits (6 times the MRHD of 200 mg/day on a mg/m^2 basis). In rabbits, the incidence of the skeletal variation, extra single rib, was increased following administration of milnacipran at 15 mg/kg/day during the period of organogenesis.

There are no adequate and well-controlled studies in pregnant women. Savella should be used during pregnancy only if the potential benefit justifies the potential risk to the fetus.

To provide information regarding the exposure to Savella during pregnancy, Physicians are advised to recommend that pregnant patients taking Savella enroll in the Savella Pregnancy Registry. Enrollment is voluntary and may be initiated by pregnant patients or their healthcare providers by contacting the registry at 1-877-643-3010 or by email at registries@kendle.com. Data forms may also be downloaded from the registry website at www.savellapregnancyregistry.com.

Nonteratogenic Effects

Neonates exposed to dual reuptake inhibitors of serotonin and norepinephrine, or selective serotonin reuptake inhibitors late in the third trimester have developed complications requiring prolonged hospitalization, respiratory support, and tube feeding. Such complications can arise immediately upon delivery. Reported clinical findings have included respiratory distress, cyanosis, apnea, seizures, temperature instability, feeding difficulty, vomiting, hypoglycemia, hypotonia, hypertonia, hyperreflexia, tremor, jitteriness, irritability, and constant crying. These features are consistent with either a direct toxic effect of these classes of drugs or, possibly, a drug discontinuation syndrome. It should be noted that, in some cases, the clinical picture is consistent with serotonin syndrome [see Warnings and Precautions (5.2)].

In rats, a decrease in pup body weight and viability on postpartum day 4 were observed when milnacipran, at a dose of 5 mg/kg/day (approximately 0.2 times the MRHD on a mg/m^2 basis), was administered orally to rats during late gestation. The no-effect dose for maternal and offspring toxicity was 2.5 mg/kg/day (approximately 0.1 times the MRHD on a mg/m^2 basis).

8.2 Labor and Delivery

The effect of milnacipran on labor and delivery is unknown. The use of Savella during labor and delivery is not recommended.

8.3 Nursing Mothers

There are no adequate and well-controlled studies in nursing mothers. It is not known if milnacipran is excreted in human milk. Studies in animals have shown that milnacipran or its metabolites are excreted in breast milk. Because many drugs are excreted in human milk and because of the potential for serious adverse reactions in nursing infants from milnacipran, a decision should be made whether to discontinue the drug, taking into account the importance of the drug to the mother. Because the safety of Savella in infants is not known, nursing while on Savella is not recommended.

8.4 Pediatric Use

Safety and effectiveness of Savella in a fibromyalgia pediatric population below the age of 17 have not been established [see Boxed Warning and Warnings and Precautions (5.1)]. The use of Savella is not recommended in pediatric patients.

8.5 Geriatric Use

In controlled clinical studies of Savella, 402 patients were 60 years or older, and no overall differences in safety and efficacy were observed between these patients and younger patients. In view of the predominant excretion of unchanged milnacipran via kidneys and the expected decrease in renal function with age, renal function should be considered prior to use of Savella in the elderly [see Dosage and Administration (2.2)].

SNRIs, SSRIs, and Savella, have been associated with cases of clinically significant hyponatremia in elderly patients, who may be at greater risk for this adverse event [see Warnings and Precautions (5.8)].

9 DRUG ABUSE AND DEPENDENCE

9.1 Controlled Substance

Milnacipran is not a controlled substance.

9.2 Abuse

Milnacipran did not produce behavioral signs indicative of abuse potential in animal or human studies.

9.3 Dependence

Milnacipran produces physical dependence, as evidenced by the emergence of withdrawal symptoms following drug discontinuation, similar to other SNRIs and SSRIs. These withdrawal symptoms can be severe. Thus, Savella should be tapered and not abruptly discontinued after extended use [see Warnings and Precautions (5.7)].

10 OVERDOSAGE

There is limited clinical experience with Savella overdose in humans. In clinical trials, cases of acute ingestions up to 1000 mg, alone or in combination with other drugs, were reported with none being fatal.

In postmarketing experience, fatal outcomes have been reported for acute overdoses primarily involving multiple drugs but also with Savella only. The most common signs and symptoms included increased blood pressure, cardio-respiratory arrest, changes in the level of consciousness (ranging from somnolence to coma), confusional state, dizziness, and increased hepatic enzymes.

Management of Overdose

There is no specific antidote to Savella, but if serotonin syndrome ensues, specific treatment (such as with cyproheptadine and/or temperature control) may be considered. In case of acute overdose, treatment should consist of those general measures employed in the management of overdose with any drug.

An adequate airway, oxygenation, and ventilation should be assured and cardiac rhythm and vital signs should be monitored. Induction of emesis is not recommended. Gastric lavage with a large-bore orogastric tube with appropriate airway protection, if needed, may be indicated if performed soon after ingestion or in symptomatic patients. Because there is no specific antidote for Savella, symptomatic care and treatment with gastric lavage and activated charcoal should be considered as soon as possible for patients who experience a Savella overdose.

Due to the large volume of distribution of this drug, forced diuresis, dialysis, hemoperfusion, and exchange transfusion are unlikely to be beneficial.

In managing overdose, the possibility of multiple drug involvement should be considered. The physician should consider contacting a poison control center for additional information on the treatment of any overdose. Telephone numbers for certified poison control centers are listed in the Physicians' Desk Reference (PDR).

11 DESCRIPTION

Milnacipran hydrochloride is a selective norepinephrine and serotonin reuptake inhibitor; it inhibits norepinephrine uptake with greater potency than serotonin. It is a racemic mixture with the chemical name: (±)-[1R(S),2S(R)]-2-(aminomethyl)-N,N-diethyl-1-phenylcyclopropanecarboxamide hydrochloride. The structural formula is:

Milnacipran hydrochloride is a white to off-white crystalline powder with a melting point of 179°C. It is freely soluble in water, methanol, ethanol, chloroform, and methylene chloride and sparingly soluble in diethyl ether. It has an empirical formula of C15H23ClN2O and a molecular weight of 282.8 g/mol.

Savella is available for oral administration as film-coated tablets containing 12.5 mg, 25 mg, 50 mg, and 100 mg milnacipran hydrochloride. Each tablet also contains dibasic calcium phosphate, povidone, carboxymethylcellulose calcium, colloidal silicon dioxide, magnesium stearate, and talc as inactive ingredients. Additionally, the following inactive ingredients are also present as components of the film coat:

12.5 mg:

FD&C Blue #2 Aluminum Lake, hypromellose, polyethylene glycol, titanium dioxide

25 mg:

Hypromellose, polyethylene glycol, titanium dioxide

50 mg:

Hypromellose, polyethylene glycol, titanium dioxide

100 mg:

FD&C Red #40 Aluminum Lake, hypromellose, polyethylene glycol, titanium dioxide

12 CLINICAL PHARMACOLOGY

12.1 Mechanism of Action

The exact mechanism of the central pain inhibitory action of milnacipran and its ability to improve the symptoms of fibromyalgia in humans are unknown. Preclinical studies have shown that milnacipran is a potent inhibitor of neuronal norepinephrine and serotonin reuptake; milnacipran inhibits norepinephrine uptake with approximately 3-fold higher potency in vitro than serotonin without directly affecting the uptake of dopamine or other neurotransmitters. Milnacipran has no significant affinity for serotonergic (5-HT1-7), α- and β-adrenergic, muscarinic (M1-5), histamine (H1-4), dopamine (D1-5), opiate, benzodiazepine, and ү-aminobutyric acid (GABA) receptors in vitro. Pharmacologic activity at these receptors is hypothesized to be associated with the various anticholinergic, sedative, and cardiovascular effects seen with other psychotropic drugs. Milnacipran has no significant affinity for Ca++, K+, Na+ and Cl- channels and does not inhibit the activity of human monoamine oxidases (MAO-A and MAO-B) or acetylcholinesterase.

12.2 Pharmacodynamics

Cardiovascular Electrophysiology-The effect of Savella on the QTcF interval was measured in a double-blind placebo- and positive-controlled parallel study in 88 healthy subjects using 600 mg/day Savella (3 to 6 times the recommended therapeutic dose for fibromyalgia). After baseline and placebo adjustment, the maximum mean QTcF change was 8 ms (2-sided 90% CI, 3-12 ms). This increase is not considered to be clinically significant.

12.3 Pharmacokinetics

Milnacipran is well absorbed after oral administration with an absolute bioavailability of approximately 85% to 90%. The exposure to milnacipran increased proportionally within the therapeutic dose range. It is excreted predominantly unchanged in urine (55%) and has a terminal elimination half-life of about 6 to 8 hours. Steady-state levels are reached within 36 to 48 hours and can be predicted from single-dose data. The active enantiomer, d-milnacipran, has a longer elimination half-life (8-10 hours) than the l-enantiomer (4-6 hours). There is no interconversion between the enantiomers.

Absorption and Distribution

Savella is absorbed following oral administration with maximum concentrations (Cmax) reached within 2 to 4 hours post dose. Absorption of Savella is not affected by food. The absolute bioavailability is approximately 85% to 90%. The mean volume of distribution of milnacipran following a single intravenous dose to healthy subjects is approximately 400 L. Plasma protein binding is 13%.

Metabolism and Elimination

Milnacipran and its metabolites are eliminated primarily by renal excretion. Following oral administration of ^14C-milnacipran hydrochloride, approximately 55% of the dose was excreted in urine as unchanged milnacipran (24% as l-milnacipran and 31% as d-milnacipran). The l-milnacipran carbamoyl-O-glucuronide was the major metabolite excreted in urine and accounted for approximately 17% of the dose; approximately 2% of the dose was excreted in urine as d-milnacipran carbamoyl-O-glucuronide. Approximately 8% of the dose was excreted in urine as the N-desethyl milnacipran metabolite.

Pharmacokinetics in Special Populations

Renal Impairment-Milnacipran pharmacokinetics were evaluated following single oral administration of 50 mg Savella to subjects with mild (creatinine clearance [CLcr] 50-80 mL/min), moderate (CLcr 30-49 mL/min), and severe (CLcr 5-29 mL/min) renal impairment and to healthy subjects (CLcr > 80 mL/min). The mean AUC0-∞ increased by 16%, 52%, and 199%, and terminal elimination half-life increased by 38%, 41%, and 122% in subjects with mild, moderate, and severe renal impairment, respectively, compared with healthy subjects.

No dosage adjustment is necessary for patients with mild renal impairment. Caution should be exercised in patients with moderate renal impairment. Dose adjustment is necessary in severe renal impairment patients [see Dosage and Administration (2.2)].

Hepatic Impairment-Milnacipran pharmacokinetics were evaluated following single oral administration of 50 mg Savella to subjects with mild (Child-Pugh A), moderate (Child-Pugh B), and severe (Child-Pugh C) hepatic impairment and to healthy subjects. AUC0-∞ and T½ were similar in healthy subjects and subjects with mild and moderate hepatic impairment. However, subjects with severe hepatic impairment had a 31% higher AUC0-∞ and a 55% higher T½ than healthy subjects. Caution should be exercised in patients with severe hepatic impairment.

Elderly-Cmax and AUC parameters of milnacipran were about 30% higher in elderly (> 65 years) subjects compared with young subjects due to age-related decreases in renal function. No dosage adjustment is necessary based on age unless renal function is severely impaired [see Dosage and Administration (2.2)].

Gender-Cmax and AUC parameters of milnacipran were about 20% higher in female subjects compared with male subjects. Dosage adjustment based on gender is not necessary.

Drug-Drug Interactions

In Vitro Studies

In general, milnacipran, at concentrations that were at least 25 times those attained in clinical trials, did not inhibit human CYP1A2, CYP2A6, CYP2C9, CYP2C19, CYP2D6, CYP2E1, and CYP3A4 or induce human CYP1A2, CYP2B6, CYP2C8, CYP2C9, CYP2C19, and CYP3A4/5 enzyme systems, indicating a low potential of interactions with drugs metabolized by these enzymes.

In vitro studies have shown that the biotransformation rate of milnacipran by human hepatic microsomes and hepatocytes was low. A low biotransformation was also observed following incubation of milnacipran with cDNA-expressed human CYP1A2, CYP2A6, CYP2B6, CYP2C9, CYP2C19, CYP2D6, CYP2E1, and CYP3A4 isozymes.

In Vivo Studies

The drug interaction studies described in this section were conducted in healthy adult subjects.

Carbamazepine-There were no clinically significant changes in the pharmacokinetics of milnacipran following co-administration of Savella (100 mg/day) and carbamazepine (200 mg twice a day). No changes were observed in the pharmacokinetics of carbamazepine or its epoxide metabolite due to co-administration with Savella.

Clomipramine-Switching from clomipramine (75 mg once a day) to milnacipran (100 mg/day) without a washout period did not lead to clinically significant changes in the pharmacokinetics of milnacipran. Because an increase in adverse events (eg, euphoria and postural hypotension) was observed after switching from clomipramine to milnacipran, monitoring of patients during treatment switch is recommended.

Digoxin-There was no pharmacokinetic interaction between Savella (200 mg/day) and digoxin (0.2 mg/day Lanoxicaps) following multiple-dose administration to healthy subjects.

Fluoxetine-Switching from fluoxetine (20 mg once a day), a strong inhibitor of CYP2D6 and a moderate inhibitor of CYP2C19, to milnacipran (100 mg/day) without a washout period did not affect the pharmacokinetics of milnacipran.

Lithium-Multiple doses of Savella (100 mg/day) did not affect the pharmacokinetics of lithium.

Lorazepam-There was no pharmacokinetic interaction between a single dose of Savella (50 mg) and lorazepam (1.5 mg).

Pregabalin-There were no clinically significant changes in the steady-state pharmacokinetics of milnacipran or pregabalin following twice a day co-administration of 50 mg milnacipran and 150 mg pregabalin.

Warfarin-Steady-state milnacipran (200 mg/day) did not affect the pharmacokinetics of R-warfarin and S-warfarin or the pharmacodynamics (as assessed by measurement of prothrombin INR) of a single dose of 25 mg warfarin. The pharmacokinetics of Savella were not altered by warfarin.

13 NONCLINICAL TOXICOLOGY

13.1 Carcinogenesis, Mutagenesis, and Impairment of Fertility

Carcinogenesis

Dietary administration of milnacipran to rats at doses of 50 mg/kg/day (2 times the MRHD on a mg/m^2 basis) for 2 years caused a statistically significant increase in the incidence of thyroid C-cell adenomas and combined adenomas and carcinomas in males. A carcinogenicity study was conducted in Tg.rasH2 mice for 6 months at oral gavage doses of up to 125 mg/kg/day. Milnacipran did not induce tumors in Tg.rasH2 mice at any dose tested.

Mutagenesis

Milnacipran was not mutagenic in the in vitro bacterial reverse mutation assay (Ames test) or in the L5178Y TK +/- mouse lymphoma forward mutation assay. Milnacipran was also not clastogenic in an in vitro chromosomal aberration test in human lymphocytes or in the in vivo mouse micronucleus assay.

Impairment of Fertility

Although administration of milnacipran to male and female rats had no statistically significant effect on mating or fertility at doses up to 80 mg/kg/day (4 times the MRHD on an mg/m^2 basis), there was an apparent dose-related decrease in the fertility index at clinically relevant doses based on body surface area.

13.2 Animal Toxicology and Pharmacology

Hepatic Effects

Chronic administration (2 years) of milnacipran to rats at 15 mg/kg (0.6 times the MRHD on an mg/m^2 basis) and higher doses showed increased incidences of centrilobular vacuolation of the liver in male rats and eosinophilic foci in male and female rats in the absence of any change in hepatic enzymes. The clinical significance of the finding is not known. Chronic (1 year) administration in the primate at doses up to 25 mg/kg (2 times the MRHD on a mg/m^2 basis) did not demonstrate similar evidence of hepatic changes.

Ocular Effects

Chronic (2 years) administration of milnacipran to rats at 15 mg/kg (0.6 times the MRHD on a mg/m^2 basis) and higher doses showed increased incidence of keratitis of the eye. One-year studies in the rat and primate did not show this response.

14 CLINICAL STUDIES

Management of Fibromyalgia

The efficacy of Savella for the management of fibromyalgia was established in two double-blind, placebo-controlled, multicenter studies in adult patients (18-74 years of age). Enrolled patients met the American College of Rheumatology (ACR) criteria for fibromyalgia (a history of widespread pain for 3 months and pain present at 11 or more of the 18 specific tender point sites). Approximately 35% of patients had a history of depression. Study 1 was six months in duration and Study 2 was three months in duration.

A larger proportion of patients treated with Savella than with placebo experienced a simultaneous reduction in pain from baseline of at least 30% (VAS) and also rated themselves as much improved or very much improved based on the patient global assessment (PGIC). In addition, a larger proportion of patients treated with Savella met the criteria for treatment response, as measured by the composite endpoint that concurrently evaluated improvement in pain (VAS), physical function (SF-36 PCS), and patient global assessment (PGIC), in fibromyalgia as compared to placebo.

Study 1: This 6-month study compared total daily doses of Savella 100 mg and 200 mg to placebo. Patients were enrolled with a minimum mean baseline pain score of ≥ 50 mm on a 100 mm visual analog scale (VAS) ranging from 0 ("no pain") to 100 ("worst possible pain"). The mean baseline pain score in this trial was 69. The efficacy results for Study 1 are summarized in Figure 1.

Figure 1 shows the proportion of patients achieving various degrees of improvement in pain from baseline to the 3-month time point and who concurrently rated themselves globally improved (PGIC score of 1 or 2). Patients who did not complete the 3-month assessment were assigned 0% improvement. More patients in the Savella treatment arms experienced at least a 30% reduction in pain from baseline (VAS) and considered themselves globally improved (PGIC) than did patients in the placebo arm. Treatment with Savella 200 mg/day did not confer greater benefit than treatment with Savella 100 mg/day.

Figure 1: Patients Achieving Various Levels of Pain Relief with Concurrent Ratings of Being Much or Very Much Improved on the PGIC — Study 1

Study 2: This 3-month study compared total daily doses of Savella 100 mg and 200 mg to placebo. Patients were enrolled with a minimum mean baseline pain score of ≥ 40 mm on a 100-mm VAS ranging from 0 ("no pain") to 100 ("worst possible pain"). The mean baseline pain score in this trial was 65. The efficacy results for Study 2 are summarized in Figure 2.

Figure 2 shows the proportion of patients achieving various degrees of improvement in pain from baseline to the 3-month time point and who concurrently rated themselves globally improved (PGIC score of 1 or 2). Patients who did not complete the 3-month assessment were assigned 0% improvement. More patients in the Savella treatment arms experienced at least a 30% reduction in pain from baseline (VAS) and considered themselves globally improved (PGIC) than did patients in the placebo arm. Treatment with Savella 200 mg/day did not confer greater benefit than treatment with Savella 100 mg/day.

Figure 2: Patients Achieving Various Levels of Pain Relief with Concurrent Ratings of Being Much or Very Much Improved on the PGIC — Study 2

In both studies, some patients who rated themselves as globally "much" or "very much" improved experienced a decrease in pain as early as week 1 of treatment with a stable dose of Savella that persisted throughout these studies.

16 HOW SUPPLIED/STORAGE AND HANDLING

50-mg tablets:

White, oval-shaped, film-coated tablets, debossed with "FL" on one side and "50" on the reverse

Bottles of 60 | NDC 54868-6043-0
Bottles of 180 | NDC 54868-6043-1

100-mg tablets:

Pink, oval-shaped, film-coated tablets, debossed with "FL" on one side and "100" on the reverse

Bottles of 60 | NDC 54868-6024-0

Storage

Store at 25°C (77°F); excursions permitted between 15°C and 30°C (between 59°F and 86°F) [See USP Controlled Room Temperature].

17 PATIENT COUNSELING INFORMATION

See Medication Guide

17.1 Information in Medication Guide

Prescribers or other health professionals should inform patients, their families, and their caregivers about the benefits and risks associated with treatment with Savella and should counsel them in its appropriate use. A patient Medication Guide is available for Savella. The prescriber or health professional should instruct patients, their families, and their caregivers to read the Medication Guide and should assist them in understanding its contents. Patients should be given the opportunity to discuss the contents of the Medication Guide and to obtain answers to any questions they may have. The complete text of the Medication Guide is reprinted at the end of this document.

Patients should be advised of the following issues and asked to alert their prescriber if these occur while taking Savella:

17.2 Suicide Risk

Patients and their families and caregivers should be advised that Savella is a selective norepinephrine and serotonin reuptake inhibitor and therefore belongs to the same class of drugs as antidepressants. Patients, their families, and their caregivers should be advised that patients with depression may be at increased risk for clinical worsening and/or suicidal ideation if they stop taking anti-depressant medication, change the dose, or start a new medication.

Patients, their families, and their caregivers should be encouraged to be alert to the emergence of anxiety, agitation, panic attacks, insomnia, irritability, hostility, aggressiveness, impulsivity, akathisia (psychomotor restlessness), hypomania, or other unusual changes in behavior, worsening of depression, and suicidal ideation, especially early during treatment with Savella or other drugs that inhibit the reuptake of norepinephrine and/or serotonin, and when the dose is adjusted up or down. Families and caregivers of patients should be advised to observe for the emergence of such symptoms on a day-to-day basis, since changes may be abrupt. Such symptoms should be reported to the patient's prescriber or health professional, especially if they are severe, abrupt in onset, or were not part of the patient's presenting symptoms [see Boxed Warning and Warnings and Precautions (5.1)].

17.3 Serotonin Syndrome

Patients should be cautioned about the risk of serotonin syndrome with concomitant use of Savella and triptans, tramadol, or other serotonergic agents [see Warnings and Precautions (5.2)].

17.4 Effect on Blood Pressure and Pulse

Patients should be advised that their blood pressure and pulse should be monitored at regular intervals when receiving treatment with Savella [see Warnings and Precautions (5.3, 5.4)].

17.5 Abnormal Bleeding

Patients should be cautioned about the concomitant use of Savella and NSAIDs, aspirin, or other drugs that affect coagulation, since the combined use of agents that interfere with serotonin reuptake and these agents has been associated with an increased risk of abnormal bleeding [see Warnings and Precautions (5.9)].

17.6 Ability to Drive and Use Machinery

Savella might diminish mental and physical capacities necessary to perform certain tasks such as operating machinery, including motor vehicles. Patients should be cautioned about operating machinery or driving motor vehicles until they are reasonably certain that Savella treatment does not affect their ability to engage in such activities.

17.7 Alcohol

Patients should be advised to avoid consumption of alcohol while taking Savella [see Warnings and Precautions (5.6, 5.13)].

17.8 Discontinuation

Patients should be advised that withdrawal symptoms can occur when discontinuing treatment with Savella, particularly when discontinuation is abrupt [see Warnings and Precautions (5.7)].

17.9 Pregnancy

Patients should be advised to notify their physician if they become pregnant or intend to become pregnant during Savella therapy [see Use in Specific Populations (8.1)].

Patients should be encouraged to enroll in the Savella Pregnancy Registry if they become pregnant, preferably before any prenatal testing is done. This registry is collecting information about the safety of milnacipran during pregnancy. To enroll, patients or their healthcare providers may call the toll-free number 1-877-643-3010 [see Use In Specific Populations (8.1)], download data forms from our website, www.savellapregnancyregistry.com, or email the registry for further information at registries@kendle.com.

17.10 Nursing

Patients should be advised to notify their physician if they are breast-feeding [see Use in Specific Populations (8.3)].

MEDICATION GUIDE

Savella® (Sa-vel-la) Tablets

(milnacipran HCl)

Antidepressant Medicines, Depression and other serious Mental Illnesses, and Suicidal

Thoughts or Actions

Savella is not used to treat depression, but it acts like medicines that are used to treat depression (antidepressants) and other psychiatric disorders.

Read the Medication Guide that comes with you or your family member's antidepressant medicine. This Medication Guide is only about the risk of suicidal thoughts or actions with antidepressant medicines. Talk to your or your family member's healthcare provider about:

- all risks and benefits of treatment with antidepressant medicines
- all treatment choices for depression or other serious mental illness

What is the most important information I should know about antidepressant medicines, depression and other serious mental illnesses, and suicidal thoughts or actions?

1. Antidepressant medicines may increase suicidal thoughts or actions in some children, teenagers, and young adults within the first few months of treatment.
2. Depression and other serious mental illnesses are the most important causes of suicidal thoughts and actions. Some people may have a particularly high risk of having suicidal thoughts or actions. These include people who have (or have a family history of) bipolar illness (also called manic-depressive illness) or suicidal thoughts or actions.
3. How can I watch for and try to prevent suicidal thoughts and actions in myself or a family member?
  - Pay close attention to any changes, especially sudden changes, in mood, behaviors, thoughts, or feelings. This is very important when an antidepressant medicine is started or when the dose is changed.
  - Call the healthcare provider right away to report new or sudden changes in mood, behavior, thoughts, or feelings.
  - Keep all follow-up visits with the healthcare provider as scheduled. Call the healthcare provider between visits as needed, especially if you have concerns about symptoms.

Call a healthcare provider right away if you or your family member has any of the following symptoms, especially if they are new, worse, or worry you:

- thoughts about suicide or dying
- attempts to commit suicide
- new or worse depression
- new or worse anxiety
- feeling very agitated or restless
- panic attacks

- new or worse irritability
- acting aggressive, being angry, or violent
- acting on dangerous impulses
- an extreme increase in activity and talking (mania)
- other unusual changes in behavior or mood
- trouble sleeping (insomnia)

What else do I need to know about antidepressant medicines?

- Never stop an antidepressant medicine without first talking to a healthcare provider. Stopping an antidepressant medicine suddenly can cause other symptoms.
- Antidepressants are medicines used to treat depression and other illnesses. It is important to discuss all the risks of treating depression and also the risks of not treating it. Patients and their families or other caregivers should discuss all treatment choices with the healthcare provider, not just the use of antidepressants.
- Antidepressant medicines have other side effects. Talk to the healthcare provider about the side effects of the medicine prescribed for you or your family member.
- Antidepressant medicines can interact with other medicines. Know all of the medicines that you or your family member takes. Keep a list of all medicines to show the healthcare provider. Do not start new medicines without first checking with your healthcare provider.
- Not all antidepressant medicines prescribed for children are FDA approved for use in children. Talk to your child's healthcare provider for more information. Call your doctor for medical advice about side effects. You may report side effects to FDA at 1-800-FDA-1088.

This Medication Guide has been approved by the U.S. Food and Drug Administration.

Revised: December 2009

Manufactured for:
Forest Pharmaceuticals, Inc.
Manufactured by:
Forest Laboratories, Inc.

Licensed from Pierre Fabre Medicament and Cypress Bioscience, Inc.

Relabeling and Repackaging by:
Physicians Total Care, Inc.
Tulsa, Oklahoma 74146

PACKAGE LABEL - PRINCIPAL DISPLAY PANEL - 50 MG LABEL

Rx only

Savella®

(milnacipran HCl) Tablets

50 mg

Dispense the accompanying Medication

Guide to each patient.

PACKAGE LABEL - PRINCIPAL DISPLAY PANEL - 100 MG LABEL

Rx only

Savella®

(milnacipran HCl) Tablets

100 mg

Dispense the accompanying Medication

Guide to each patient.